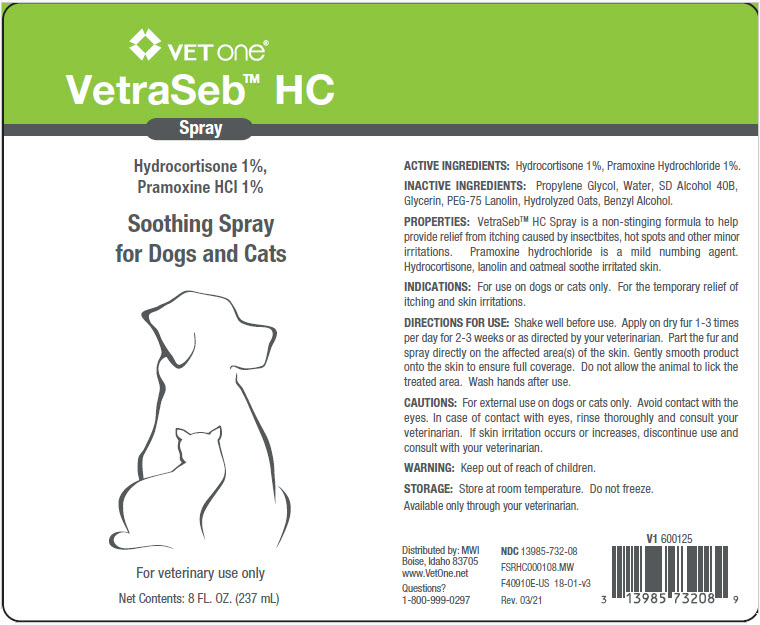 DRUG LABEL: VetraSeb
NDC: 13985-732 | Form: SPRAY
Manufacturer: MWI/VetOne
Category: animal | Type: OTC ANIMAL DRUG LABEL
Date: 20250910

ACTIVE INGREDIENTS: PRAMOXINE HYDROCHLORIDE 10 mg/1 mL; HYDROCORTISONE 10 mg/1 mL
INACTIVE INGREDIENTS: WATER; ALCOHOL; GLYCERIN; PEG-75 LANOLIN; OATMEAL; PROPYLENE GLYCOL; BENZYL ALCOHOL

DESCRIPTION

VetraSeb HC Spray

ACTIVE INGREDIENTS: Pramoxine HCI 1%, Hydrocortisone 1%.

INACTIVE INGREDIENTS: Propylene Glycol, Water, SD Alcohol 40B, Glycerin, PEG-75 Lanolin, Hydrolyzed Oats, Benzyl Alcohol.

PROPERTIES: VetraSeb™ HC Spray is a non-stinging formula to help provide relief from itching caused by insect bites, hot spots and other minor irritations. Pramoxine hydrochloride is a mild numbing agent. Hydrocortisone, lanolin and oatmeal soothe irritated skin.

INDICATIONS AND USAGE

INDICATIONS: For use on dogs and cats only. For the temporary relief of pruritus and skin irritations.

DIRECTIONS FOR USE: Shake well before use. Apply on dry fur 1-3 times per day for 2-3 weeks or as directed by your veterinarian. Part the fur and spray directly on the affected area(s) of the skin. Gently smooth product on to the skin to ensure full coverage. Do not allow the animal to lick the treated area. Wash hands after use.

WARNINGS AND PRECAUTIONS

CAUTIONS: For external use on dogs and cats only. Avoid contact with the eyes. In case of contact with eyes, rinse thoroughly and consult your veterinarian. If skin irritation occurs or increases, discontinue use and consult with your veterinarian.

WARNING: Keep out of the reach of children.

STORAGE: Store at room temperature. Do not freeze.

Available only through your veterinarian.

Distributed by: MWI

Boise, Idaho 83705

www.VetOne.net

Questions?

1-800-999-0297

PRINCIPAL DISPLAY PANEL - 237 mL Bottle Label

VET ONE®

VetraSeb™ HC

Spray

Hydrocortisone 1%,
Pramoxine HCl 1%

Soothing Spray
for Dogs and Cats

For veterinary use only

Net Contents: 8 FL. OZ. (237 mL)